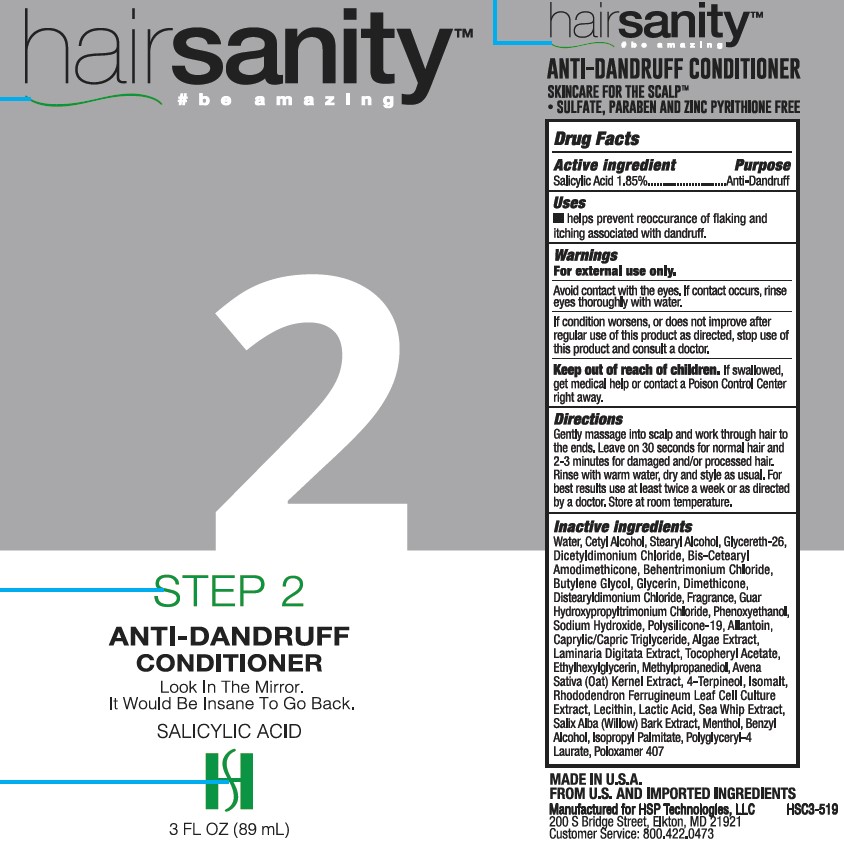 DRUG LABEL: H Plus Holdings
NDC: 58443-0247 | Form: RINSE
Manufacturer: Prime Enterprises
Category: otc | Type: HUMAN OTC DRUG LABEL
Date: 20211028

ACTIVE INGREDIENTS: SALICYLIC ACID 18.13 mg/1 mL
INACTIVE INGREDIENTS: ISOMALT; ALCOHOL; BEHENTRIMONIUM CHLORIDE; STEARYL ALCOHOL; OAT; PHYMATOLITHON CALCAREUM; ISOPROPYL ALCOHOL; .ALPHA.-TOCOPHEROL ACETATE; DIMETHICONE; BENZYL ALCOHOL; ISOPROPYL PALMITATE; MENTHOL; WATER; BUTYLENE GLYCOL; LECITHIN, SOYBEAN; POLOXAMER 407; WILLOW BARK; PSEUDOPTEROGORGIA ELISABETHAE; ETHYLHEXYLGLYCERIN; GLYCERETH-26; GLYCERIN; RHODODENDRON FERRUGINEUM LEAF; 4-TERPINEOL, (+/-)-; ALLANTOIN; METHYLPROPANEDIOL; PHENOXYETHANOL; SODIUM HYDROXIDE; GUAR HYDROXYPROPYLTRIMONIUM CHLORIDE (1.7 SUBSTITUENTS PER SACCHARIDE); MEDIUM-CHAIN TRIGLYCERIDES; DIPROPYLENE GLYCOL; LAMINARIA DIGITATA; CETYL ALCOHOL; DISTEARYLDIMONIUM CHLORIDE

H Plus 1.85% Salicylic Acid Anti-Dandruff Conditioner 3 Fl. Oz.

Active Ingredients

Salicylic Acid 1.85%

Purpose

Anti-Dandruff

Uses

helps prevent reoccurance of flaking and itching associated with dandruff.

Warnings

For external use only.

WHEN USING

Avoid contact wih the eyes. If contact occurs, rinse eyes thoroughly with water.

ASK DOCTOR

If condition worsens, or does not improve after regular use of this product as directed, stop use of this product and consult a doctor.

Keep out of reach of children. If swallowed, get medical help or contact a Posion Control Center right away.

Directions

Gently massage into scalp and work through hair to the ends. Leave on 30 seconds for normal hair and 2-3 minutes for damaged and/or processed hair. Rinse with warm water, dry and style as usual. For best results use at least twice a week or as directed by a doctor. Store at room temperature.

Inactive Ingredients

Water, Cetyl Alcohol, Stearyl Alcohol, Glycereth-26, Bis-Cetearyl Amodimethicone, Dicetyldimonium Chloride, Behentrimonium Chloride, Butylene Glycol, Glycerin, Dimethicone, Distearyldimonium Chloride, Fragrance, Guar Hydroxypropyltrimonium Chloride, Phenoxyethanol, Isopropyl Alcohol, Sodium Hydroxide, Alcohol Denat., Caprylic/Capric Triglyceride, Tocopheryl Acetate, Allantoin, Dipropylene Glycol, Polysilicone-19, Ethylhexylglycerin, Methylpropanediol, Avena Sativa (Oat) Kernel Extract, 4-Terpineol, Lecithin, Isopropyl Palmitate, Poloxamer 407, Isomalt, Algae Extract, Salix Alba (Willow) Bark Extract, Sea Whip Extract, Polyglyceryl-4 Laurate, Menthol, Benzyl Alcohol, Laminaria Digitata Extract, Rhododendron Ferrugineum Leaf Cell Culture Extract